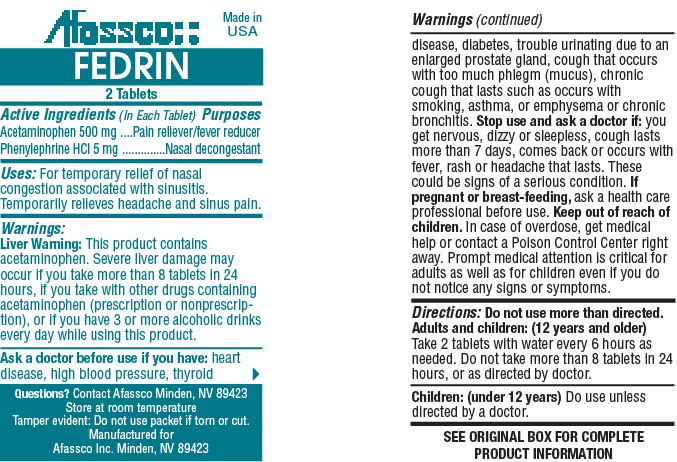 DRUG LABEL: Fedrin
NDC: 51532-0140 | Form: TABLET
Manufacturer: Afassco Inc.
Category: otc | Type: HUMAN OTC DRUG LABEL
Date: 20191218

ACTIVE INGREDIENTS: ACETAMINOPHEN 500 1/1 1; PHENYLEPHRINE HYDROCHLORIDE 5 1/1 1
INACTIVE INGREDIENTS: STARCH, CORN; POVIDONE; FD&C BLUE NO. 1; STEARIC ACID; SODIUM STARCH GLYCOLATE TYPE A CORN; MICROCRYSTALLINE CELLULOSE

Drug Facts

Active Ingredients (In Each Tablet)

Acetaminophen 500 mg, Phenylephrine HCl 5 mg

PURPOSE

Pain reliever/fever reducer, Nasal decongestant

Uses:

For temporary relief of nasal congestion associated with sinusitis.

Temporarily relieves headache and sinus pain.

Warnings:

Liver Warning: This product contains acetaminophen. Severe liver damage may occur if you take more than 8 tablets in 24 hours, if you take with other drugs containing acetaminophen (prescription or nonprescription), or if you have 3 or more alcoholic drinks every day while using this product.

Ask a doctor before use if you have: heart disease, high blood pressure, thyroid disease, diabetes, trouble urinating due to an enlarged prostate gland, cough that occurs with too much phlegm (mucus), chronic cough that lasts such as occurs with smoking, asthma, or emphysema or chronic bronchitis.

Stop use and ask a doctor if: you get nervous, dizzy or sleepless, cough lasts more than 7 days, comes back or occurs with fever, rash or headache that lasts. These could be signs of a serious condition.

PREGNANCY OR BREAST FEEDING

If pregnant or breast-feeding, ask a health care professional before use.

Keep out of reach of children.

OVERDOSAGE

In case of overdose, get medical help or contact a Poison Control Center right away. Prompt medical attention is critical for adults as well as for children even if you do not notice any signs or symptoms.

DOSAGE AND ADMINISTRATION

Directions: Do not use more than directed.

Adults and children: (12 years and older) Take 2 tablets with water every 6 hours as needed. Do not take more than 8 tablets in 24 hours, or as directed by doctor.

Children: (under 12 years)

Do use unless directed by a doctor.

INACTIVE INGREDIENT

SEE ORIGINAL BOX FOR COMPLETE PRODUCT INFORMATION

PACKAGE LABEL

res